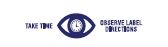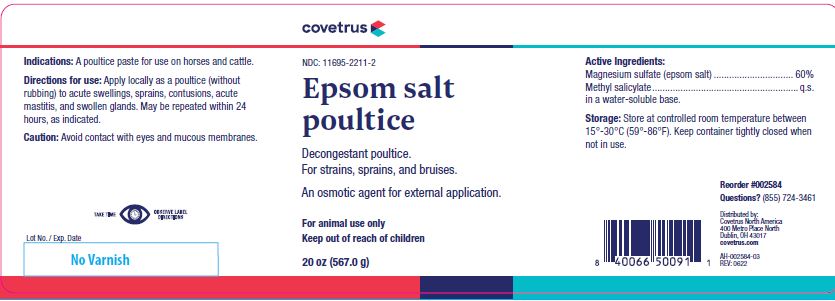 DRUG LABEL: Epsom Salt Poultice
NDC: 11695-2211 | Form: POULTICE
Manufacturer: Butler Animal health Supply, LLC dba Covetrus North America
Category: animal | Type: OTC ANIMAL DRUG LABEL
Date: 20241029

ACTIVE INGREDIENTS: MAGNESIUM SULFATE HEPTAHYDRATE 600.5 mg/1 g; METHYL SALICYLATE 10 mg/1 g

Epsom salt
poultice

STATEMENT OF IDENTITY

Decongestant poultice.
For strains, sprains, and bruises.
An osmotic agent for external application.

KEEP OUT OF REACH OF CHILDREN

For animal use only
Keep out of reach of children

HOW SUPPLIED

20 oz (567.0 g)

Indications:

A poultice paste for use on horses and cattle.

Directions for use:

Apply locally as a poultice (without rubbing) to acute swellings, sprains, contusions, acute mastitis, and swollen glands. May be repeated within 24 hours, as indicated.

Caution:

Avoid contact with eyes and mucous membranes.

Active Ingredients:

Magnesium sulfate (epsom salt) ............................... 60%
Methyl salicylate......................................................... q.s.

INACTIVE INGREDIENT

in a water-soluble base.

Storage:

Store at controlled room temperature between 15°-30°C (59°-86°F). Keep container tightly closed when not in use.

INFORMATION FOR OWNERS/CAREGIVERS

Reorder #002584
Questions? (855) 724-3461
Distributed by:
Covetrus North America
400 Metro Place North
Dublin, OH 43017
covetrus.com

AH-002584-03
REV: 0622